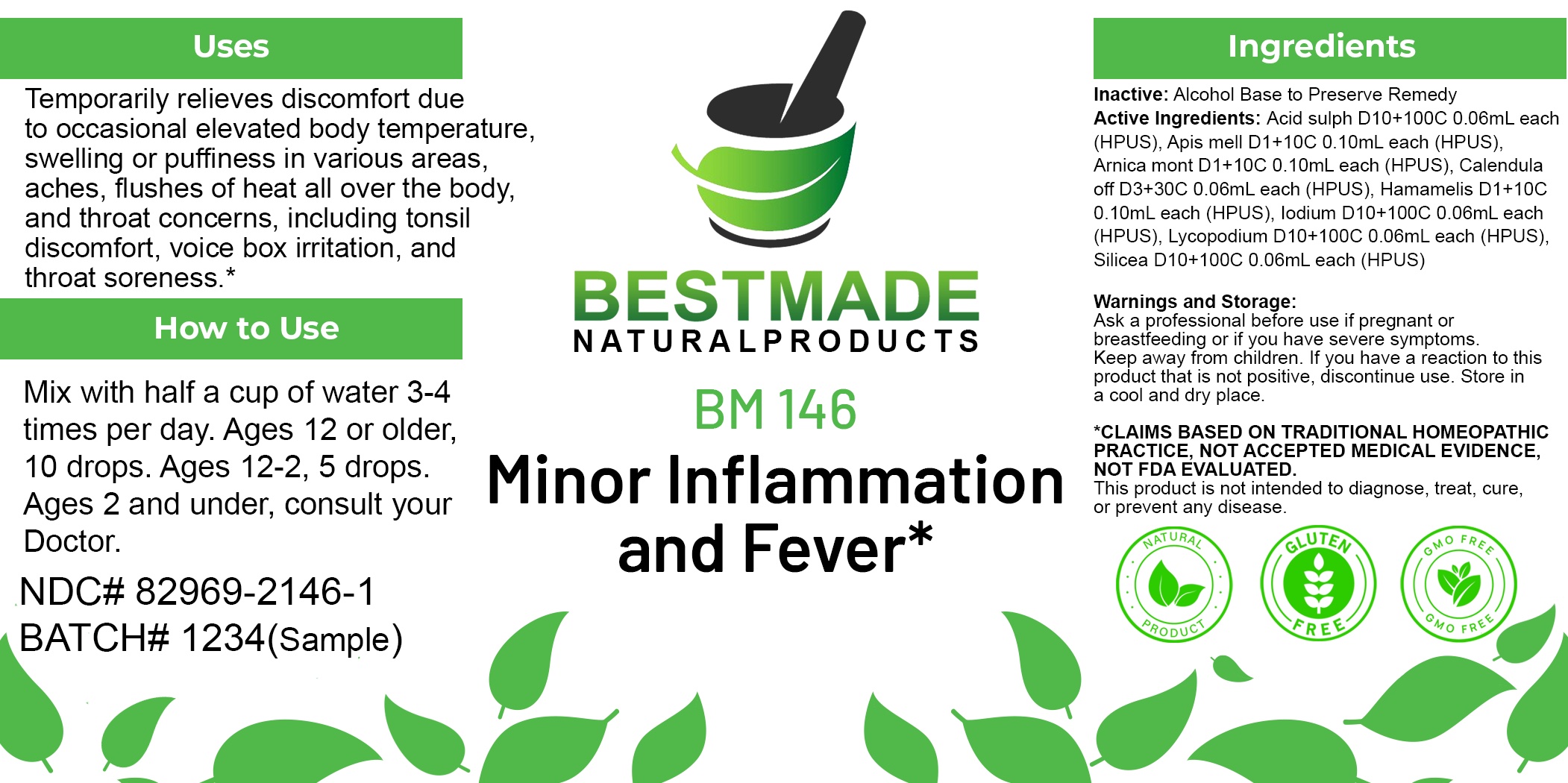 DRUG LABEL: Bestmade Natural Products BM146
NDC: 82969-2146 | Form: LIQUID
Manufacturer: Bestmade Natural Products
Category: homeopathic | Type: HUMAN OTC DRUG LABEL
Date: 20250218

ACTIVE INGREDIENTS: HAMAMELIS VIRGINIANA ROOT BARK/STEM BARK 30 [hp_C]/30 [hp_C]; LYCOPODIUM CLAVATUM SPORE 30 [hp_C]/30 [hp_C]; ARNICA MONTANA WHOLE 30 [hp_C]/30 [hp_C]; APIS MELLIFERA 30 [hp_C]/30 [hp_C]; IODINE 30 [hp_C]/30 [hp_C]; SILICON DIOXIDE 30 [hp_C]/30 [hp_C]; CALENDULA OFFICINALIS FLOWERING TOP 30 [hp_C]/30 [hp_C]; SULFURIC ACID 30 [hp_C]/30 [hp_C]
INACTIVE INGREDIENTS: ALCOHOL 30 [hp_C]/30 [hp_C]

BM146

DOSAGE AND ADMINISTRATION

How to Use

Mix with half a cup of water 3-4 times per day. Ages 12 or older, 10 drops. Ages 12-2, 5 drops. Ages 2 and under, consult your Doctor.

Inactive:

Alcohol Base to Preserve Product

ACTIVE INGREDIENT

INGREDIENTSAcid sulph D10+100C 0.06mL each (HPUS), Apis mell D1+10C 0.10mL each (HPUS), Arnica mont D1+10C 0.10mL each (HPUS), Calendula off D3+30C 0.06mL each (HPUS), Hamamelis D1+10C 0.10mL each (HPUS), Iodium D10+100C 0.06mL each (HPUS), Lycopodium D10+100C 0.06mL each (HPUS), Silicea D10+100C 0.06mL each (HPUS)

Uses
Temporarily relieves discomfort due to occasional elevated body temperature, swelling or puffiness in various areas, aches, flushes of heat all over the body. and throat concerns, including tonsil discomfort. voice box irritation, and throat soreness *

Uses
Temporarily relieves discomfort due to occasional elevated body temperature, swelling or puffiness in various areas, aches, flushes of heat all over the body. and throat concerns, including tonsil discomfort. voice box irritation, and throat soreness *

KEEP OUT OF REACH OF CHILDREN

Warnings and Storage:

Ask a professional before use if pregnant or breastfeeding or if you have severe symptoms.

Keep away from children. If you have a reaction to this product that is not positive, discontinue use. Store in a cool and dry place

*CLAIMS BASED ON TRADITIONAL HOMEOPATHIC PRACTICE, NOT ACCEPTED MEDICAL EVIDENCE NOT FDA EVALUATED.
This product is not intended to diagnose, treat, cure, or prevent any disease.

Warnings and Storage:

Ask a professional before use if pregnant or breastfeeding or if you have severe symptoms.

Keep away from children. If you have a reaction to this product that is not positive, discontinue use. Store in a cool and dry place

*CLAIMS BASED ON TRADITIONAL HOMEOPATHIC PRACTICE, NOT ACCEPTED MEDICAL EVIDENCE NOT FDA EVALUATED.
This product is not intended to diagnose, treat, cure, or prevent any disease.

Entire package label